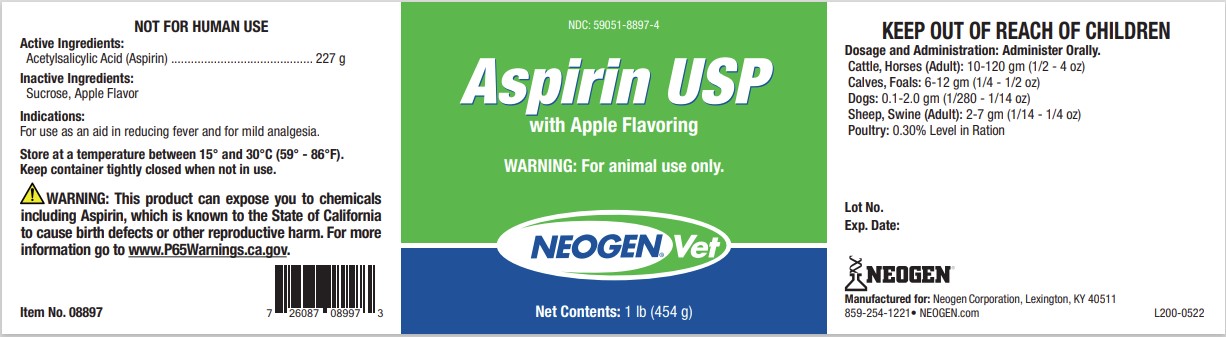 DRUG LABEL: Aspirin with Apple Flavoring
NDC: 59051-8897 | Form: POWDER
Manufacturer: Neogen Corporation - Mercer Rd.
Category: animal | Type: OTC ANIMAL DRUG LABEL
Date: 20240827

ACTIVE INGREDIENTS: ACETYLSALICYLSALICYLIC ACID 227 g/454 g
INACTIVE INGREDIENTS: SUCROSE

Active Ingredients:
Acetylsalicylic Acid (Aspirin) ........................................... 227 g

Inactive Ingredients:
Sucrose, Apple Flavor

STORAGE AND HANDLING

Store at a temperature between 15° and 30°C (59° - 86°F).
Keep container tightly closed when not in use.

Dosage and Administration: Administer Orally.
Cattle, Horses (Adult): 10-120 gm (1/2 - 4 oz)
Calves, Foals: 6-12 gm (1/4 - 1/2 oz)
Dogs: 0.1-2.0 gm (1/280 - 1/14 oz)
Sheep, Swine (Adult): 2-7 gm (1/14 - 1/4 oz)
Poultry: 0.30% Level in Ration

USER SAFETY WARNINGS

NOT FOR HUMAN USE
KEEP OUT OF REACH OF CHILDREN
WARNING: This product can expose you to chemicals
including Aspirin, which is known to the State of California
to cause birth defects or other reproductive harm. For more
information go to www.P65Warnings.ca.gov

Indications:
For use as an aid in reducing fever and for mild analgesia.

Item No. 08897

USP: 726087089973
Lot No.
Exp. Date:
NEOGEN
Manufactured for: Neogen Corporation, Lexington, KY 40511
859-254-1221• NEOGEN.com L200-0522

PACKAGE LABEL

NDC: 59051-8897-4

Aspirin USP
with Apple Flavoring

WARNING: For animal use only.

Neogen Vet

Net Contents: 1 lb (454 g)